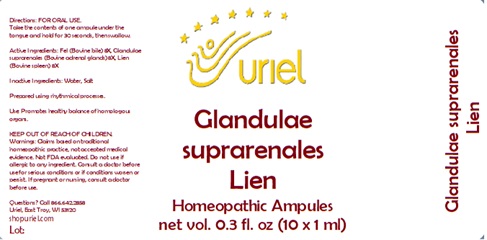 DRUG LABEL: Glandulae Suprarenales Lien
NDC: 48951-5023 | Form: LIQUID
Manufacturer: Uriel Pharmacy Inc.
Category: homeopathic | Type: HUMAN OTC DRUG LABEL
Date: 20241212

ACTIVE INGREDIENTS: BOS TAURUS GALLBLADDER 8 [hp_X]/1 mL; BOS TAURUS ADRENAL GLAND 8 [hp_X]/1 mL; BOS TAURUS SPLEEN 8 [hp_X]/1 mL
INACTIVE INGREDIENTS: WATER; SODIUM CHLORIDE

Glandulae Suprarenales Lien

INDICATIONS AND USAGE

Directions: FOR ORAL USE.

DOSAGE AND ADMINISTRATION

Take the contents of one ampule
under the tongue and hold for
30 seconds, then swallow.

ACTIVE INGREDIENT

Active Ingredients: Fel (Bovine bile) 8X, Glandulae suprarenales (Bovine adrenal glands) 8X, Lien (Bovine spleen) 8X

Inactive Ingredients: Water, Salt

Prepared using rhythmical processes.

PURPOSE

Use: Promotes healthy balance of homologous organs.

KEEP OUT OF REACH OF CHILDREN.

WARNINGS

Warnings: Claims based on traditional homeopathic practice, not accepted medical evidence. Not FDA evaluated. Do not use if allergic to any ingredient. Consult a doctor before use for serious conditions or if conditions worsen or persist. If pregnant or nursing, consult a doctor before use.

Questions? Call 866.642.2858
Uriel, East Troy, WI 53120
shopuriel.com Lot: